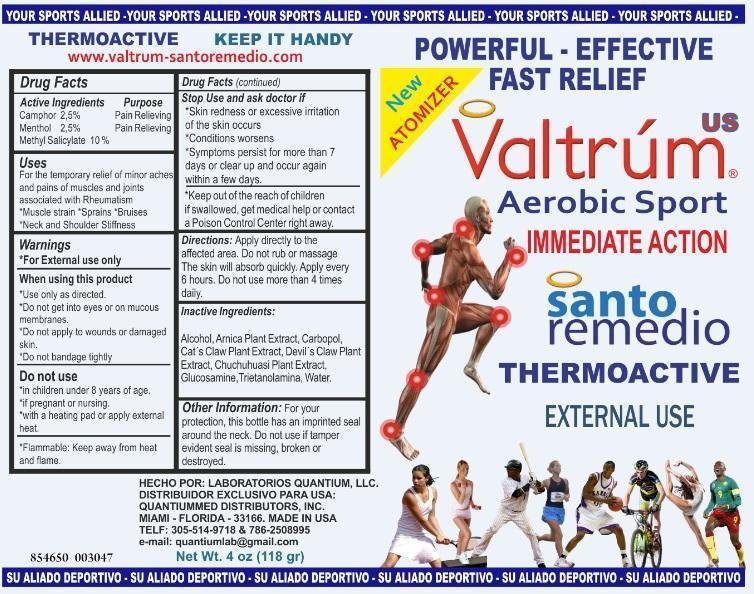 DRUG LABEL: Valtrum US Aerobic Sport IMMEDIATE ACTION
NDC: 75849-200 | Form: LIQUID
Manufacturer: Laboratorios Quantium LLC
Category: otc | Type: HUMAN OTC DRUG LABEL
Date: 20200928

ACTIVE INGREDIENTS: CAMPHOR (SYNTHETIC) 2.5 g/100 g; MENTHOL 2.5 g/100 g; METHYL SALICYLATE 10 g/100 g
INACTIVE INGREDIENTS: ALCOHOL; ARNICA MONTANA; CAT'S CLAW; HARPAGOPHYTUM PROCUMBENS ROOT; GLUCOSAMINE; TROLAMINE; WATER

Valtrúm US Soothing Topical Analgesic Ointment

Drug Facts

Active Ingredients

Camphor 2.5%

Menthol 2.5%

Purpose
Pain Relieving

USES

For the temporary relief of minor aches and pains of muscles and joints associated with

- Rheumatism
- Muscle strain
- Sprains
- Bruises
- Neck and Shoulder Stiffness

WARNINGS

For external use only

When using this product

- Use only as directed
- Do not get into eyes or on mucous membranes
- Do not apply to wounds or damaged skin
- Do not bandage tightly.

Do not use

- in children under 8 years of age
- if pregnant or nursing
- with a heating pad or apply external heat

STORAGE AND HANDLING

Flammable: Keep away from heat and flame

Stop use and ask doctor if:

- Skin redness or excessive irritation of the skin occurs
- Condition worsens
- Symptoms persist for more than 7 days or clear up and occur again within a few days

Keep out of reach of children

If swallowed, get medical help or contact a Poison Control Center right away.

Directions:

Apply directly to the affected area. Do not rub or massage. The skin will absorb quickly. Apply every 6 hours. Do not use more than 4 times daily.

Inactive Ingredients:

Alcohol, Arnica Plant Extract, Carbopol, Cat's Claw Plant Extract, Devil's Claw Plant Extract, Chuchuhuasi Plant Extract, Glucosamine, Triethanolamina, Water

Other Information:

For your protection, this bottle has an imprinted seal around the neck. Do not use if tamper evident seal is missing, broken or destroyed.

PACKAGE LABEL

POWERFUL ANALGESIC

santo remedio

Aerobic Sport

IMMEDIATE ACTION

VALTRUMUS

Thermoactive

External Analgesic

MADE BY: Laboratorios Quantium, LLC.
Exclusively Distributed For USA BY:
QUANTIUMMED DISTRIBUTORS, INC.
MIAMI - FLORIDA - 33172
TELF: 305-514-9718 AND 786-2508995
email: QUANTIUMMED GMAIL.COM
QUANTIUMLAB GMAIL.COM